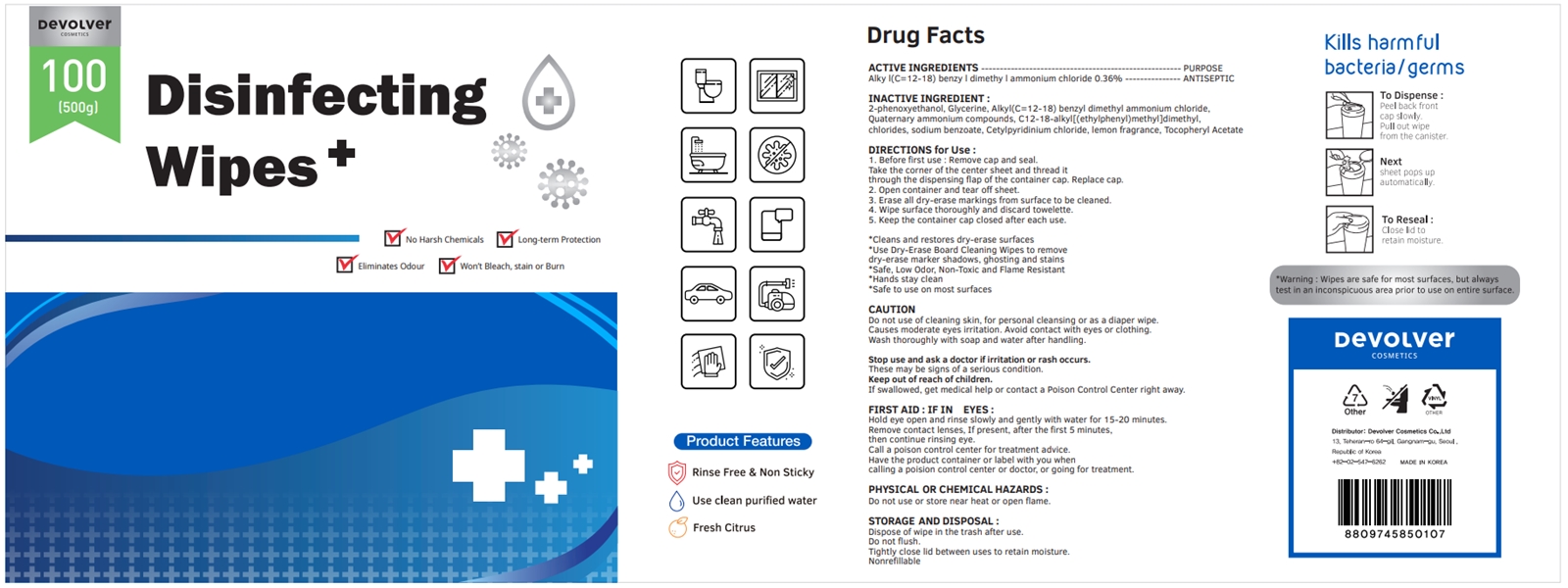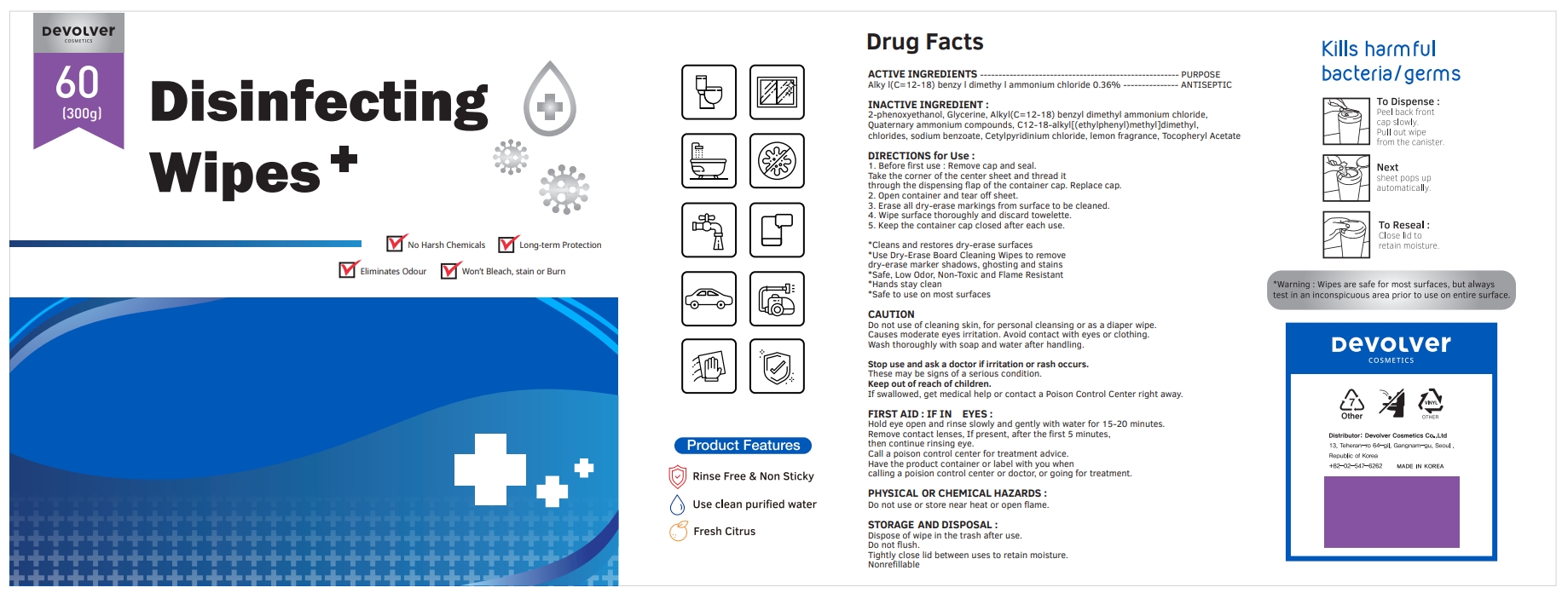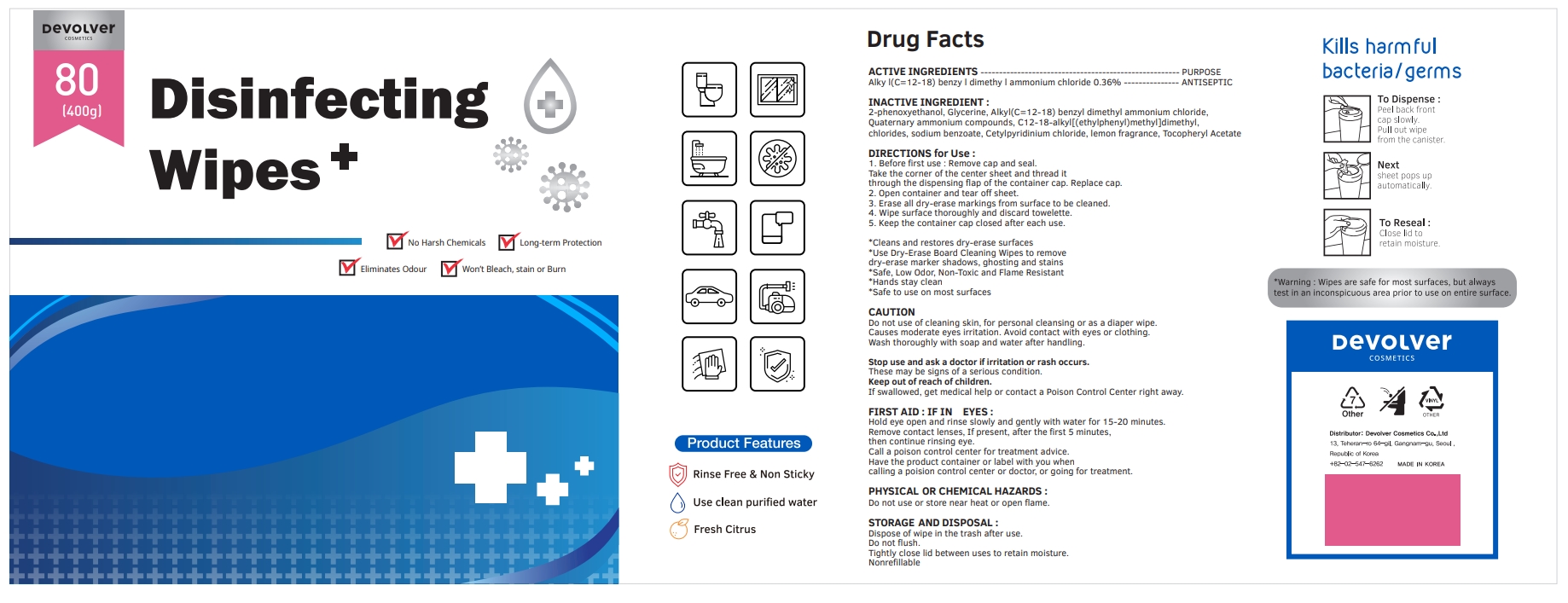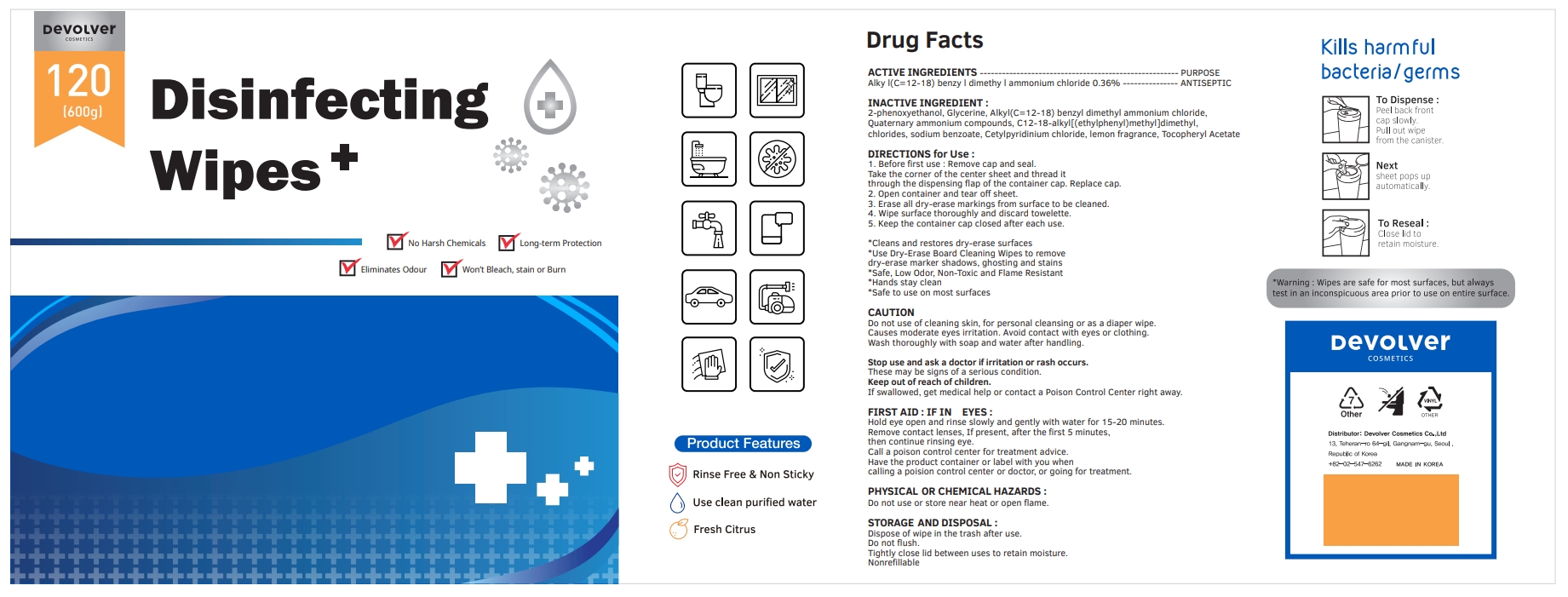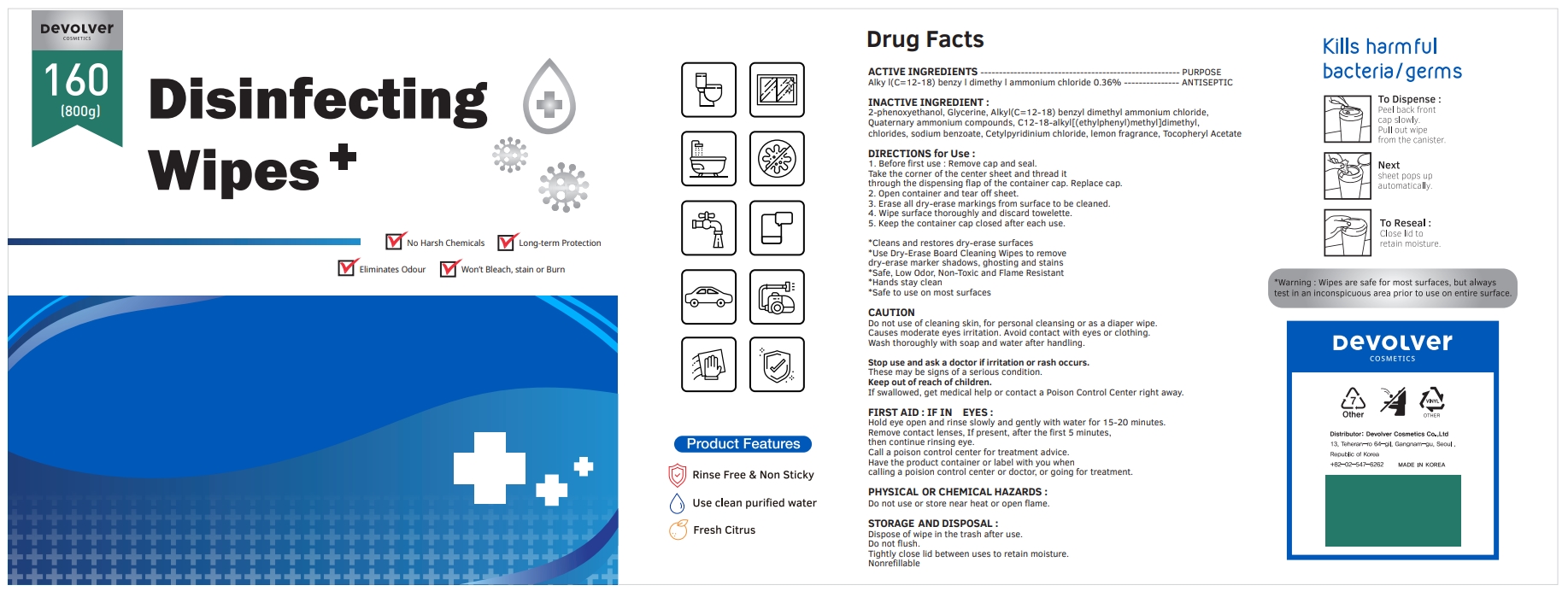 DRUG LABEL: Devolver Disinfecting Wipes
NDC: 75001-206 | Form: LIQUID
Manufacturer: Devolver Cosmetics Co., Ltd
Category: otc | Type: HUMAN OTC DRUG LABEL
Date: 20201105

ACTIVE INGREDIENTS: N-ALKYL DIMETHYL BENZYL AMMONIUM CHLORIDE (C12-C18) 0.36 g/100 g
INACTIVE INGREDIENTS: GLYCERIN; N-DIALKYL METHYL BENZYL AMMONIUM CHLORIDE (C12-C18); SODIUM BENZOATE; CETYLPYRIDINIUM CHLORIDE; FRAGRANCE LEMON ORC2001060; .ALPHA.-TOCOPHEROL ACETATE; PHENOXYETHANOL

75001-206

ACTIVE INGREDIENTS

Alkyl (C=12-18) benzyl dimethyl ammonium chloride 0.36%

PURPOSE

Antiseptic

INACTIVE INGREDIENT

2-phenoxyethanol, Glycerine, Alkyl(C=12-18) benzyl dimethyl ammonium chloride, Quaternary ammonium compounds, C12-18-alkyl[(ethylphenyl)methyl]dimethyl, chlorides, sodium benzoate, Cetylpyridinium chloride, lemon fragrance, Tocopheryl Acetate

DIRECTIONS for Use :

1. Before first use : Remove cap and seal. Take the corner of the center sheet and thread it through the dispensing flap of the container cap. Replace cap.

2. Open container and tear off sheet.

3. Erase all dry-erase markings from surface to be cleaned.

4. Wipe surface thoroughly and discard towelette.

5. Keep the container cap closed after each use.

DIRECTIONS for Use :

* Cleans and restores dry-erase surfaces

* Use Dry-Erase Board Cleaning Wipes to remove dry-erase marker shadows, ghosting and stains

* Safe, Low Odor, Non-Toxic and Flame Resistant

* Hands stay clean

* Safe to use on most surfaces

Warning :

Wipes are safe for most surfaces, but always test in an inconspicuous area prior to use on entire surface.

CAUTION

Do not use of cleaning skin, for personal cleansing or as a diaper wipe. Causes moderate eyes irritation. Avoid contact with eyes or clothing. Wash thoroughly with soap and water after handling.

CAUTION

Stop use and ask a doctor if irritation or rash occurs.

These may be signs of a serious condition.

CAUTION

Keep out of reach of children.

If swallowed, get medical help or contact a Poison Control Center right away.

FIRST AID : IF IN EYES :

Hold eye open and rinse slowly and gently with water for 15-20 minutes.

Remove contact lenses, If present, after the first 5 minutes, then continue rinsing eye.

Call a poison control center for treatment advice.

Have the product container or label with you when calling a poision control center or doctor, or going for treatment.

PHYSICAL OR CHEMICAL HAZARDS :

Do not use or store near heat or open flame.

STORAGE AND DISPOSAL :

Dispose of wipe in the trash after use.

Do not flush.

Tightly close lid between uses to retain moisture.

Nonrefillable